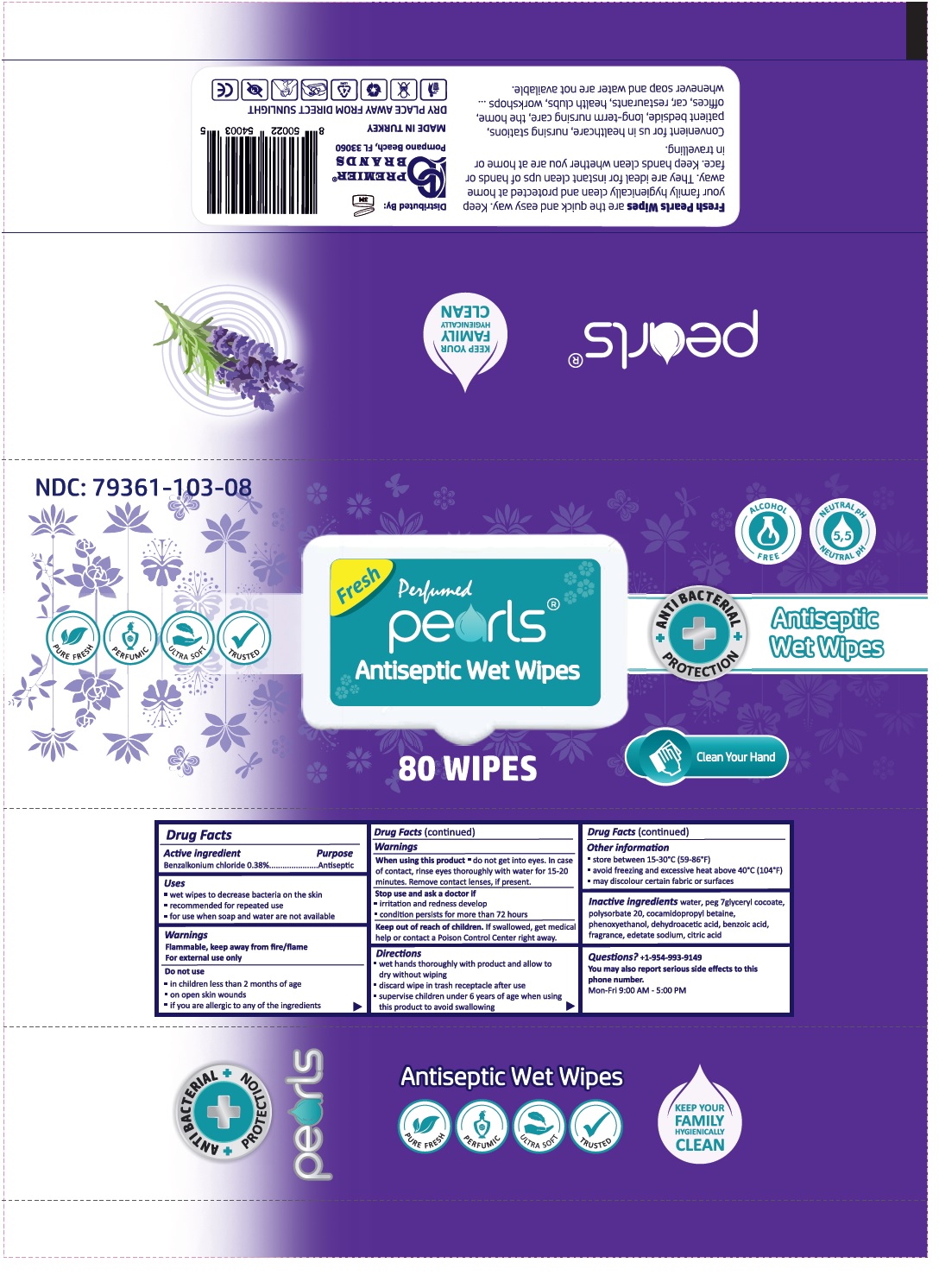 DRUG LABEL: pearls Antiseptic Wet Wipes Lavender
NDC: 79361-103 | Form: PATCH
Manufacturer: Premier Brands Usa Llc
Category: otc | Type: HUMAN OTC DRUG LABEL
Date: 20200915

ACTIVE INGREDIENTS: BENZALKONIUM CHLORIDE 0.38 g/100 g
INACTIVE INGREDIENTS: WATER; PEG-7 GLYCERYL COCOATE; POLYSORBATE 20; COCAMIDOPROPYL BETAINE; PHENOXYETHANOL; DEHYDROACETIC ACID; BENZOIC ACID; EDETATE SODIUM; CITRIC ACID MONOHYDRATE

Fresh perfumed pearls® Antiseptic wet Wipes Lavender

Active ingredient

Benzalkonium chloride 0.38%

Purpose

Antiseptic

Uses

- wet wipes to decrease bacteria on the skin
- recommended for repeated use
- for use when soap and water are not available

Warnings

Flammable, keep away from fire/flame

For external use only

Do not use

- in children less than 2 months of age
- on open skin wounds
- if you are allergic to any of the ingredients

When using this product • do not get into eyes. In case of contact, rinse eyes thoroughly with water for 15-20 minutes. Remove contact lenses, if present.

Stop use and ask a doctor if

- irritation and redness develop
- condition persists for more than 72 hours

Keep out of reach of children. If swallowed, get medical help or contact a Poison Control Center right away.

Directions

- wet hands thoroughly with product and allow to dry without wiping
- discard wipe in trash receptacle after use
- supervise children under 6 years of age when using this product to avoid swallowing

Other information

- store between 15-30°C (59-86°F)
- avoid freezing and excessive heat above 40°C (104°F)
- may discolour certain fabric or surfaces

Inactive ingredients

water, peg 7glyceryl cocoate, polysorbate 20, cocamidopropyl betaine, phenoxyethanol, dehydroaceer, peg 7glyceryl cocoate,
polysorbate 20, cocamidopropyl betaine, phenoxyethanol, dehydroacetic acid, benzoic acid, fragrance, edetate sodium, citric acid

Questions?

+1-954-993-9149
You may also report serious side effects to this phone number.
Mon-Fri 9:00 AM - 5:00 PM

PURE FRESH, PERFUMIC, ULTRA SOFT, TRUSTED

ANTIBACTERIAL PROTECTION

ALCOHOL FREE

NEUTRAL pH 5,5

Clean your Hand

KEEP YOUR FAMILY HYGIENICALLY CLEAN

Fresh Pearls Wipes are the quick and easy way. Keep your family hygienically clean and protected at home away. They are ideal for instant clean ups of hands or face. Keep hands clean whether you are at home or in travelling.
Convenient for us in healthcare, nursing stations, patient bedside, long-term nursing care, the home, offices, car, restaurants, health clubs, workshops ... whenever soap and water are not available

Distributed By:

PREMIER BRANDS USA LLC

Pompano Beach, FL 33060

MADE IN TURKEY

DRY PLACE AWAY FROM DIRECT SUNLIGHT